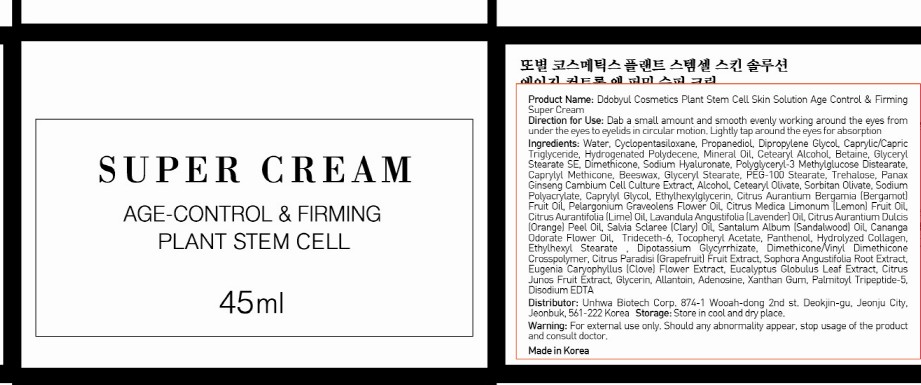 DRUG LABEL: SUPER CREAM
NDC: 50556-004 | Form: CREAM
Manufacturer: UNHWA CORPORATION
Category: otc | Type: HUMAN OTC DRUG LABEL
Date: 20100524

ACTIVE INGREDIENTS: DIMETHICONE 0.58 mL/45 mL

Drug Facts

Active Ingredient: DIMETHICONE

Inactive Ingredients:
Water, Cyclopentasiloxane, Propanediol, Dipropylene Glycol, Caprylic/Capric Triglyceride, Hydrogenated Polydecene, Mineral Oil, Cetearyl Alcohol,
Betaine, Glyceryl Stearate SE, Sodium Hyaluronate, Polyglyceryl-3 Methylglucose Distearate, Caprylyl Methicone, Beeswax, Glyceryl Stearate, PEG-100 Stearate,
Trehalose, Panax Ginseng Cambium Cell Culture Extract, Alcohol, Cetearyl Olivate, Sorbitan Olivate, Sodium Polyacrylate, Caprylyl Glycol,
Ethylhexylglycerin, Fragrance, Trideceth-6, Tocopheryl Acetate, Panthenol, Hydrolyzed Collagen, Ethylhexyl Stearate, Dipotassium Glycyrrhizate,
Dimethicone/Vinyl Dimethicone Crosspolymer, Citrus Paradisi (Grapefruit) Fruit Extract, Sophora Angustifolia Root Extract,
Eugenia Caryophyllus (Clove) Flower Extract, Eucalyptus Globulus Leaf Extract, Citrus Junos Fruit Extract, Glycerin, Allantoin, Adenosine,
Xanthan Gum, Palmitoyl Tripeptide-5, Disodium EDTA

DESCRIPTION

Direction for Use: Dab a small amount and smooth evenly working around the eyes from under the eyes to eyelids in circular motion. Lightly tap around the eyes for absorption.
Storage: Store in cool and dry place.
Warning: For external use only. Should any abnormality appear, stop usage of the product and consult doctor.